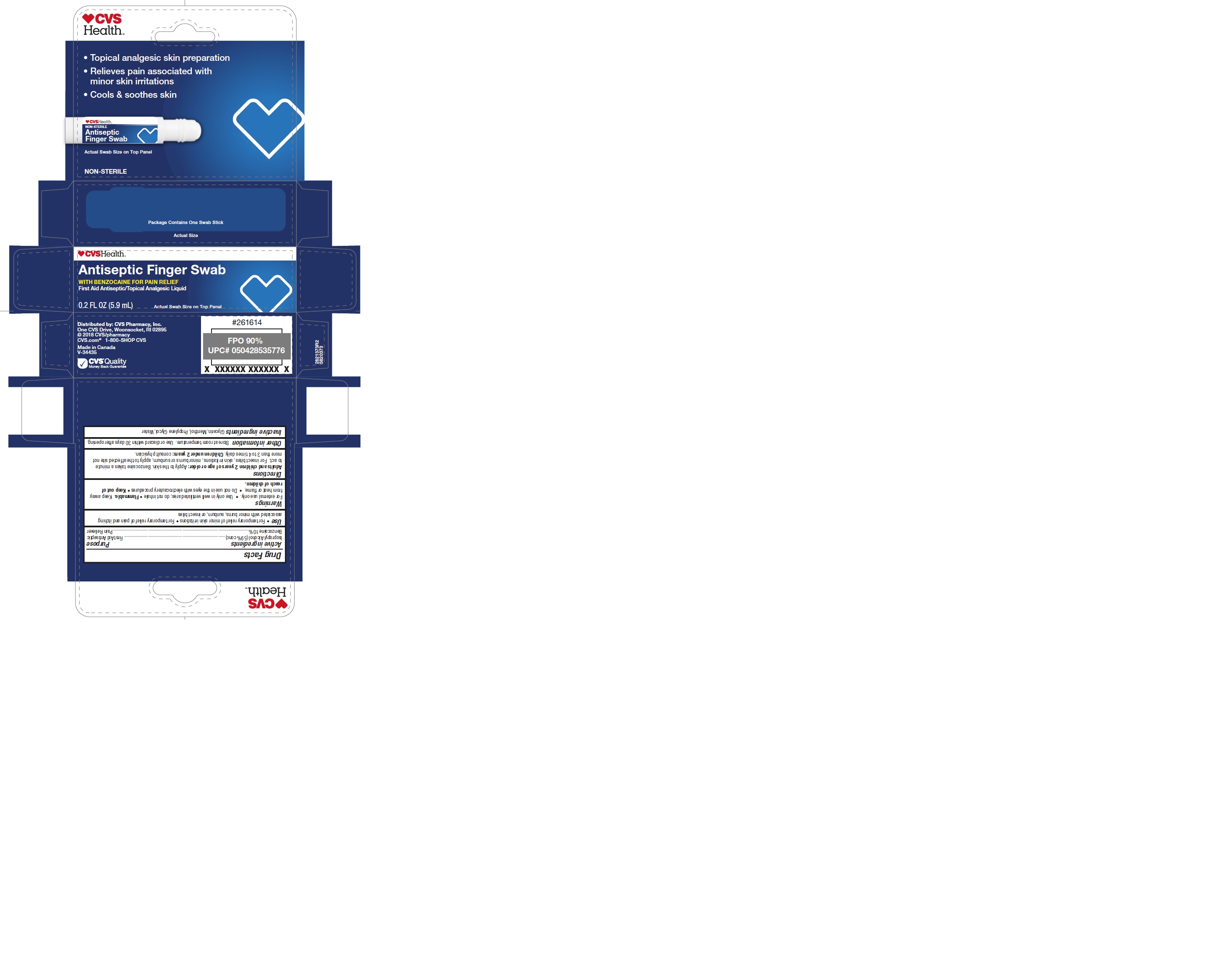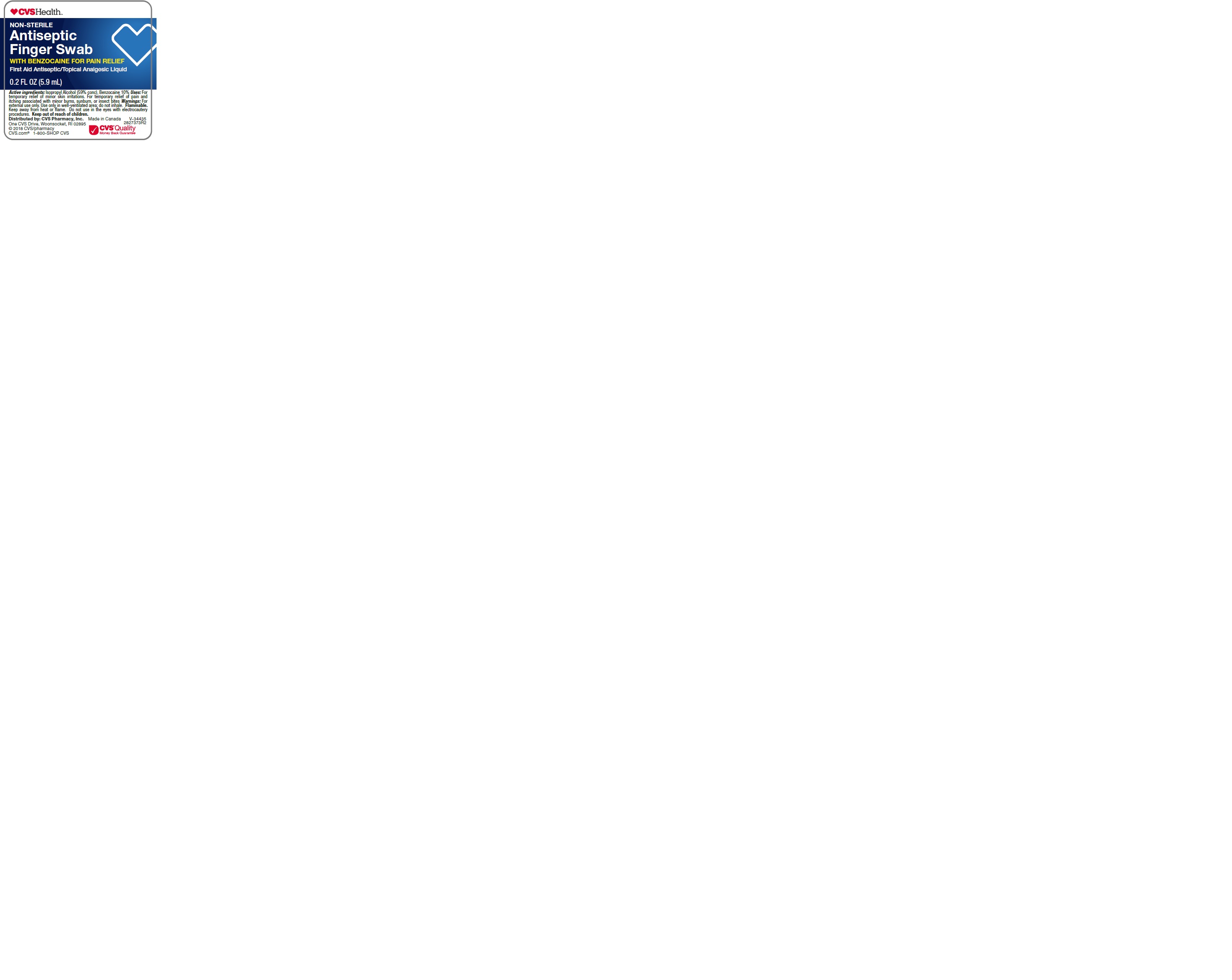 DRUG LABEL: CVS Pharmacy
NDC: 69842-873 | Form: SWAB
Manufacturer: CVS Pharmacy
Category: otc | Type: HUMAN OTC DRUG LABEL
Date: 20210810

ACTIVE INGREDIENTS: BENZOCAINE 10 g/100 mL; ISOPROPYL ALCOHOL 59 mL/100 mL
INACTIVE INGREDIENTS: WATER; GLYCERIN; MENTHOL; PROPYLENE GLYCOL

CVS Antiseptic Finger Swab

Active ingredient

Isopropyl Alcohol (59% conc) ............................................................................... First Aid Antiseptic
Benzocaine 10%...........................................................................................................Pain Reliever

Uses

• For temporary relief of minor skin irritations • For temporary relief of pain and itching
associated with minor burns, sunburn, or insect bites

WARNINGS

For external use only. • Use only in well ventilated area; do not inhale • Flammable. Keep away
from heat or flame. • Do not use in the eyes with electrocautery procedures • Keep out of
reach of children.

• Keep out of reach of children.

Directions

Adults and children 2 years of age or older: Apply to the skin. Benzocaine takes a minute
to act. For insect bites, skin irritations, minor burns or sunburn, apply to the affected site not
more than 3 to 4 times daily. Children under 2 years: consult physician.

Other Information

Store at room temperature. Use or discard within 30 days after opening.

Inactive ingredients

Glycerin, Menthol, Propylene Glycol, Water

DOSAGE AND ADMINISTRATION

Apply to the skin. Benzocaine takes a minute
to act. For insect bites, skin irritations, minor burns or sunburn, apply to the affected site not
more than 3 to 4 times daily.

PACKAGE LABEL

mm1.jpg

mm2.jpg